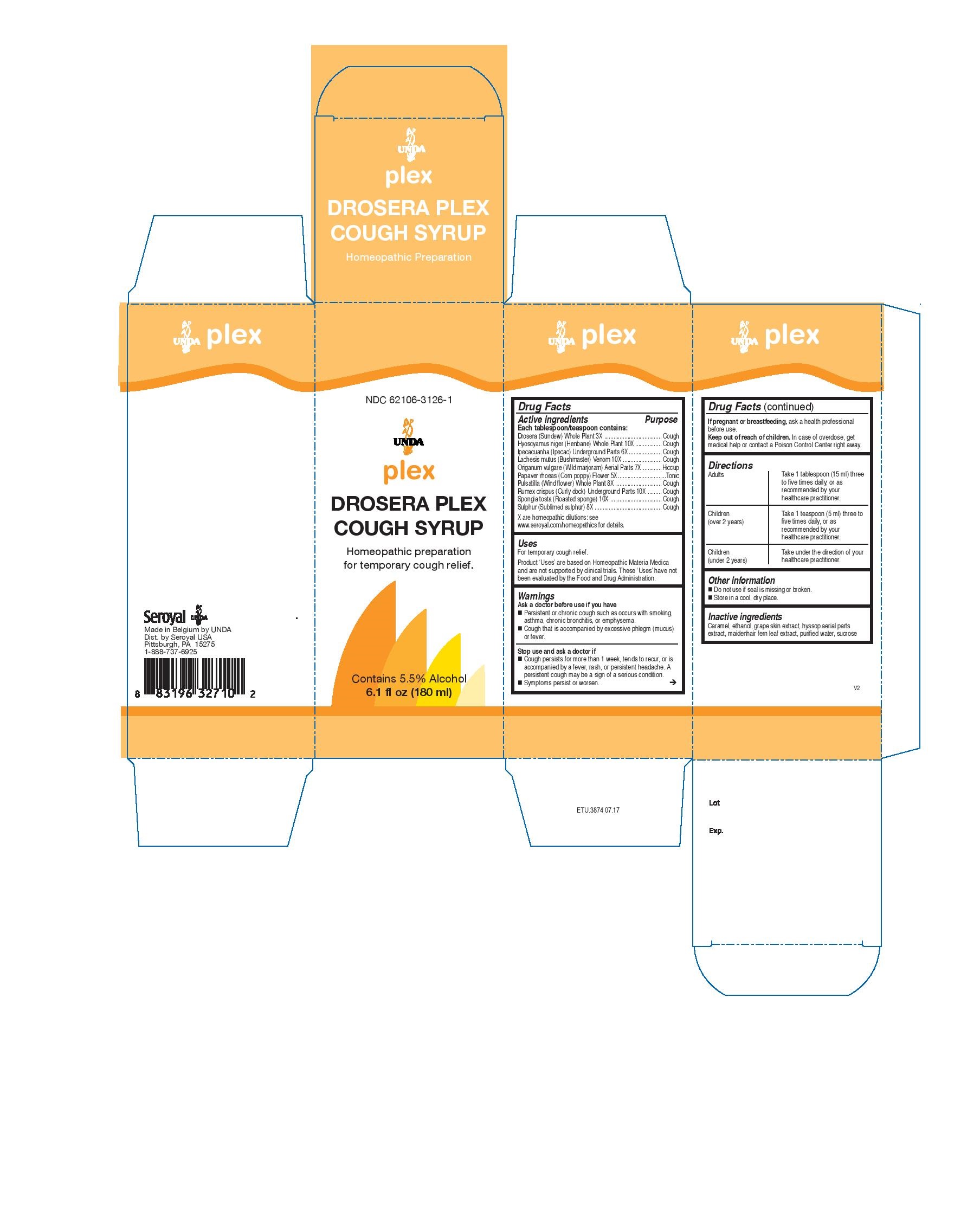 DRUG LABEL: Drosera Plex
NDC: 62106-3126 | Form: SYRUP
Manufacturer: Seroyal USA
Category: homeopathic | Type: HUMAN OTC DRUG LABEL
Date: 20221109

ACTIVE INGREDIENTS: PULSATILLA PRATENSIS 8 [hp_X]/180 mL; SPONGIA OFFICINALIS SKELETON, ROASTED 10 [hp_X]/180 mL; HYOSCYAMUS NIGER 10 [hp_X]/180 mL; LACHESIS MUTA VENOM 10 [hp_X]/180 mL; PAPAVER RHOEAS FLOWER 5 [hp_X]/180 mL; DROSERA ROTUNDIFOLIA 3 [hp_X]/180 mL; OREGANO FLOWERING TOP 7 [hp_X]/180 mL; SULFUR 8 [hp_X]/180 mL; IPECAC 6 [hp_X]/180 mL; RUMEX CRISPUS ROOT 10 [hp_X]/180 mL
INACTIVE INGREDIENTS: CARAMEL; VITIS VINIFERA ANTHOCYANINS; ADIANTUM CAPILLUS-VENERIS LEAF; SUCROSE; ALCOHOL; HYSSOPUS OFFICINALIS FLOWERING TOP; WATER

Drosera Plex Cough Syrup

Active ingredients
Each tablespoon/teaspoon contains:
Drosera (Sundew) Whole Plant 3X
Hyoscyamus niger (Henbane) Whole Plant 10X
Ipecacuanha (Ipecac) Underground Parts 6X
Lachesis mutus (Bushmaster) Venom 10X
Origanum vulgare (Wild marjoram) Aerial Parts 7X
Papaver rhoeas (Corn poppy) Flower 5X
Pulsatilla (Wind flower) Whole Plant 8X
Rumex crispus (Curly dock) Underground Parts 10X
Spongia tosta (Roasted sponge) 10X
Sulphur (Sublimed sulphur) 8X

Uses
For temporary cough relief.

Warnings
Ask a doctor before use if you have
Persistent or chronic cough such as occurs with smoking, asthma, chronic bronchitis, or emphysema.
Cough that is accompanied by excessive phlegm (mucus) or fever.
Stop use and ask a doctor if
Cough persists for more than 1 week, tends to recur, or is accompanied by a fever, rash, or persistent headache. A
persistent cough may be a sign of a serious condition.

Symptoms persist or worsen.

If pregnant or breastfeeding, ask a health professional
before use.
Keep out of reach of children. In case of overdose, get
medical help or contact a Poison Control Center right away.

PREGNANCY OR BREAST FEEDING

If pregnant or breastfeeding, ask a health professional before use.

Keep out of reach of children. In case of overdose, get
medical help or contact a Poison Control Center right away.

Directions
Adults

Take 1 tablespoon (15 ml) three to five times daily, or as recommended by your healthcare practitioner.

Children (over 2 years)

Take 1 teaspoon (5 ml) three to five times daily, or as recommended by your healthcare practitioner.
Children (under 2 years)

Take under the direction of your healthcare practitioner.

Uses
For temporary cough relief.

Directions
Adults

Take 1 tablespoon (15 ml) three to five times daily, or as recommended by your healthcare practitioner.

Children (over 2 years)

Take 1 teaspoon (5 ml) three to five times daily, or as recommended by your healthcare practitioner.
Children (under 2 years)

Take under the direction of your healthcare practitioner.

Other information
Do not use if seal is missing or broken.
Store in a cool, dry place.

Inactive ingredients
Caramel, ethanol, grape skin extract, hyssop aerial parts extract, maidenhair fern leaf extract, purified water, sucrose

PACKAGE LABEL

NDC 62106-3126-1

UNDA

plex

DROSERA PLEX COUGH SYRUP

Homeopathic preparation

for temporary cough relief.

Contains 5.5% Alcohol

6.1 fl oz (180 ml)